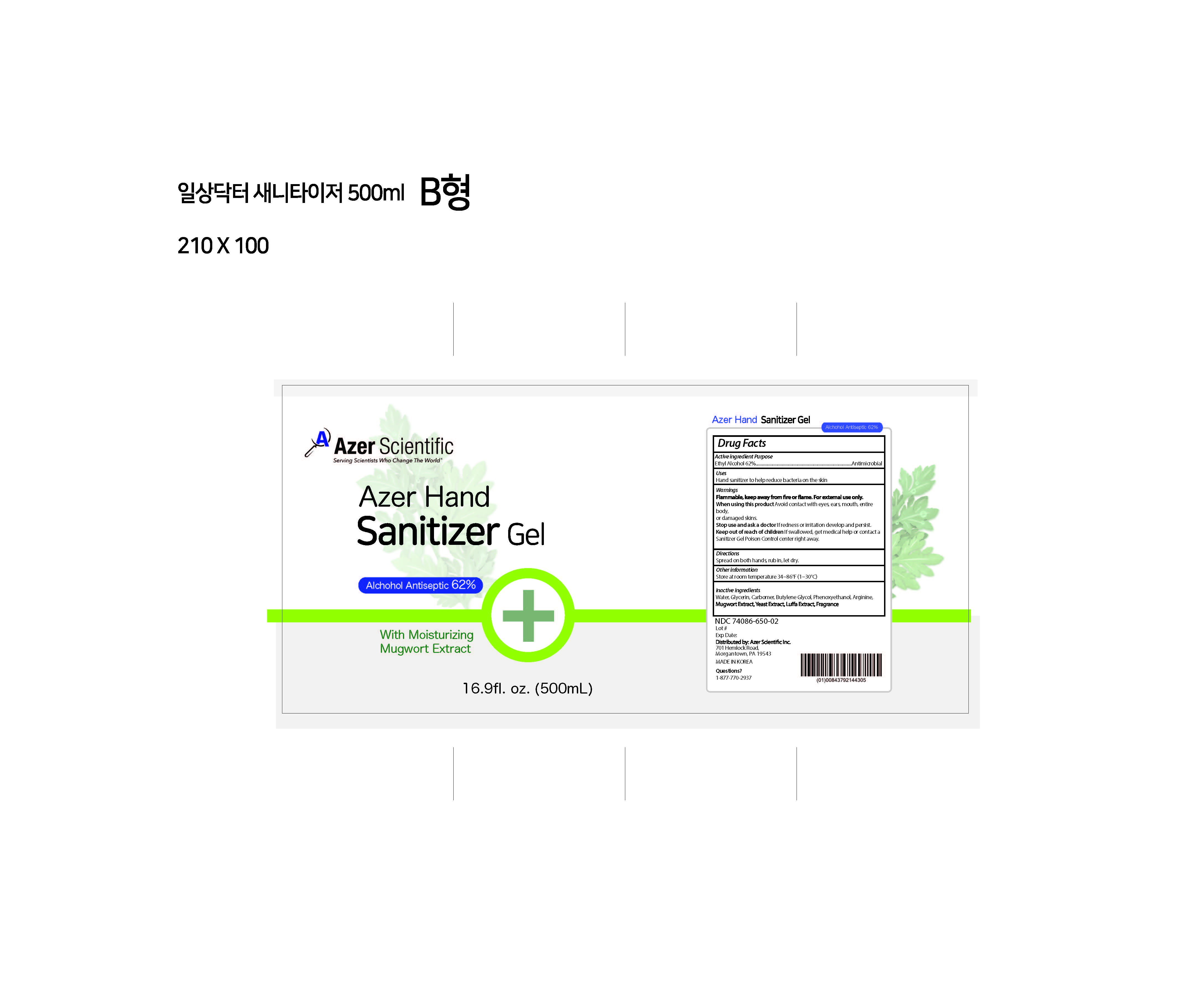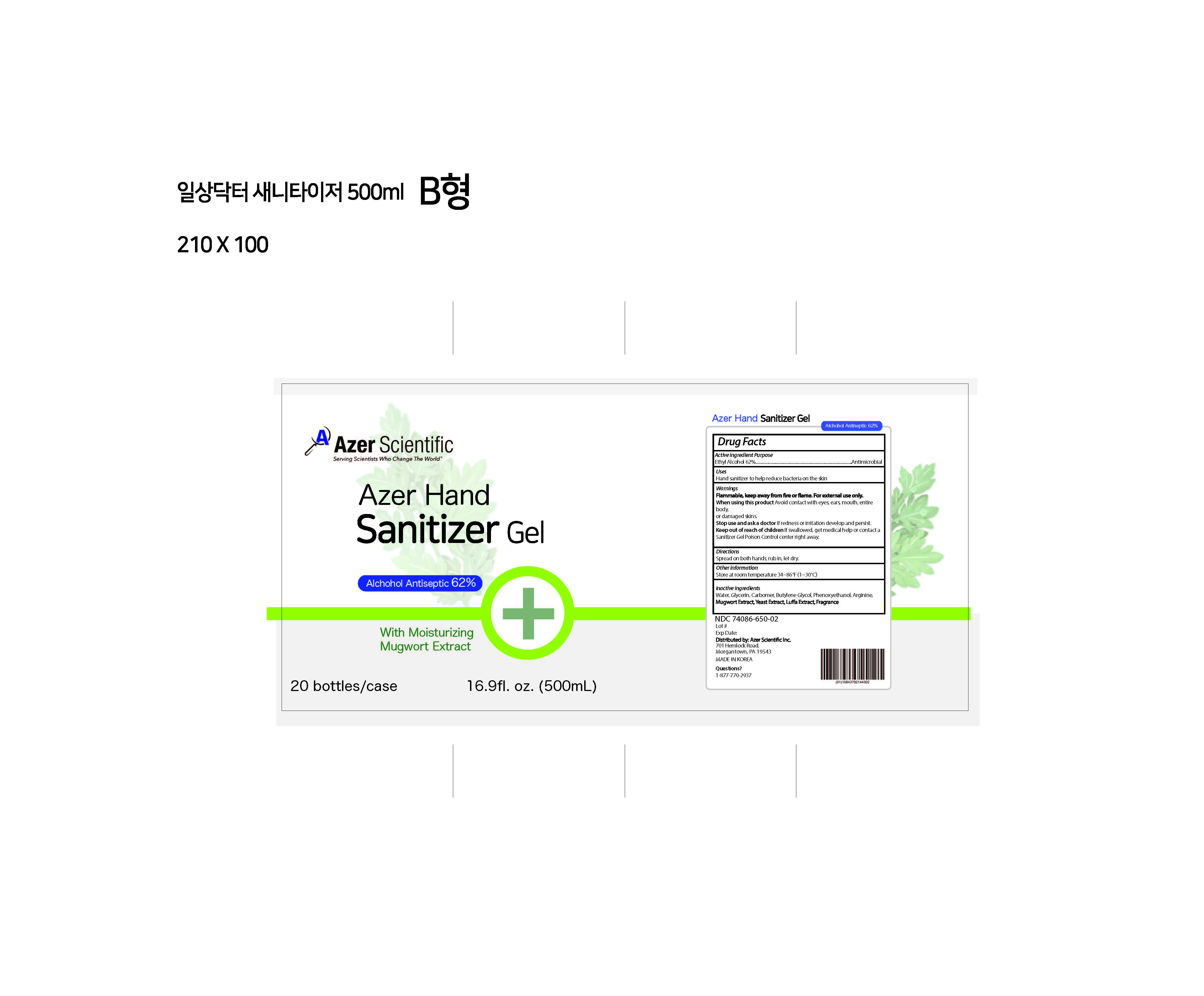 DRUG LABEL: Azer Hand Sanitizer
NDC: 74086-650 | Form: GEL
Manufacturer: Azer Scientific, Inc.
Category: otc | Type: HUMAN OTC DRUG LABEL
Date: 20200406

ACTIVE INGREDIENTS: ALCOHOL 62 mL/100 mL
INACTIVE INGREDIENTS: BUTYLENE GLYCOL; PHENOXYETHANOL; YEAST, UNSPECIFIED; ARGININE; CARBOMER 940; GLYCERIN; ARTEMISIA PRINCEPS LEAF; WATER; LUFFA

Azer Hand Sanitizer

Active Ingredient(s)

Alcohol 62% v/v. Purpose: Antimicrobial

Use

Hand Sanitizer to help reduce bacteria on the skin

Warnings

Flammable, keep away from fire or flame. For external use only.

When using this product Avoid contact with eyes, ears, mouth, entire body, or damaged skins.
Stop use and ask a doctor If redness or irritation develop and persist.
Keep out of reach of children If swallowed, get medical help or contact a Sanitizer Gel Poison Control center right away.

Directions

- Spread on both hands, rub in, let dry.

Dosage and administration changes

Change from COVID template to match current labeling

Other information

- Store at room temperature 34~86°F (1~30°C)

Inactive ingredients

Water, Glycerin, Carbomer, Butylene Glycol, Phenoxyethanol, Arginine, Mugwort Extract, Yeast Extract, Luffa Extract, Fragrance

Keep out of reach of children

Purpose

Hand sanitizer to help reduce bacteria on the skin

Package Label - Principal Display Panel

16.9 fl. oz. (500 mL) NDC: 74086-650-02